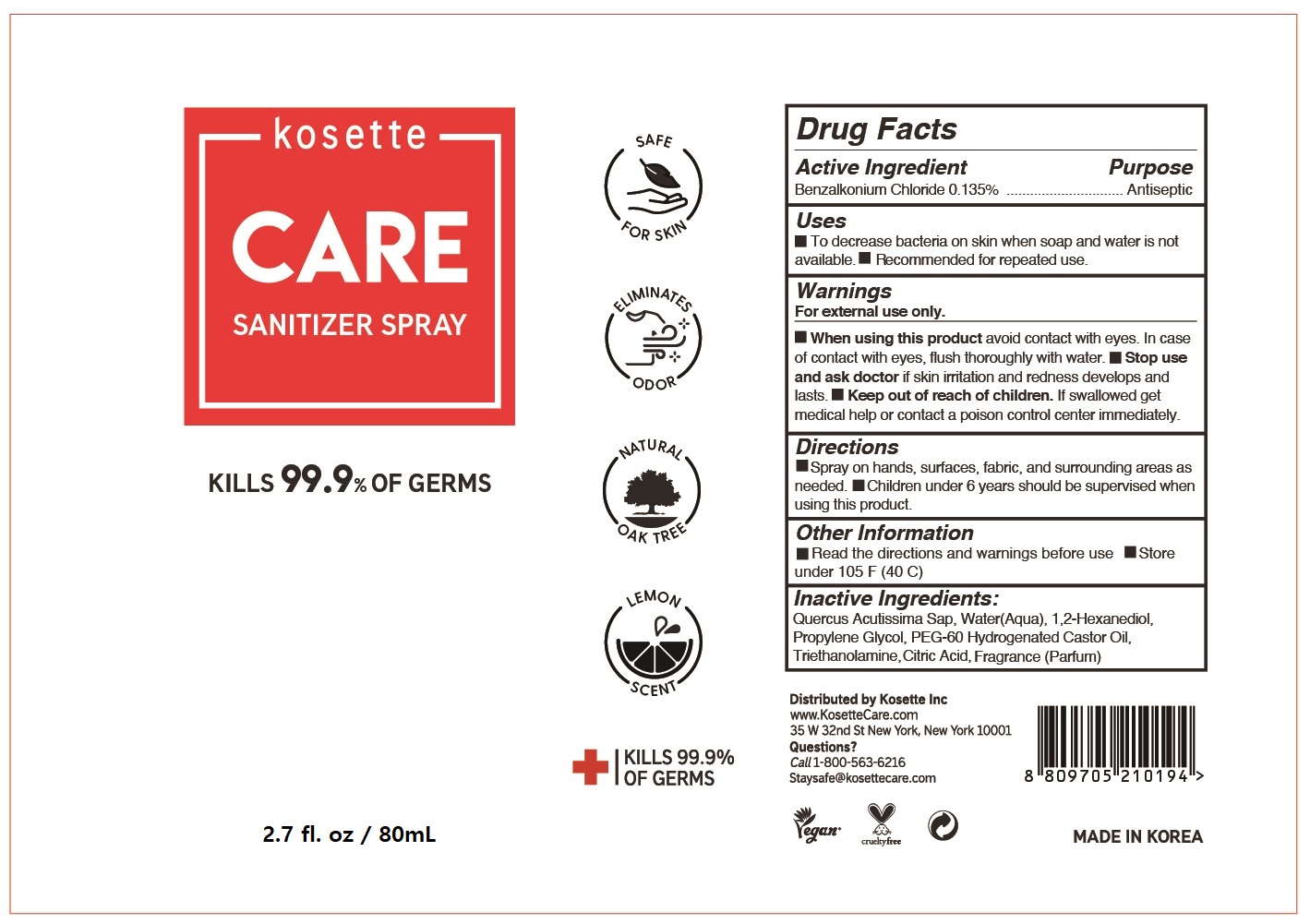 DRUG LABEL: Kosette Care Sanitizer
NDC: 79369-100 | Form: SPRAY
Manufacturer: Kosette
Category: otc | Type: HUMAN OTC DRUG LABEL
Date: 20200707

ACTIVE INGREDIENTS: BENZALKONIUM CHLORIDE 0.135 g/100 mL
INACTIVE INGREDIENTS: WATER; 1,2-HEXANEDIOL; QUERCUS ACUTISSIMA WHOLE; PROPYLENE GLYCOL; PEG-60 HYDROGENATED CASTOR OIL; TROLAMINE; ANHYDROUS CITRIC ACID

Kosette Care Sanitizer Spray (BKC)

Active Ingredients

Benzalkonium chloride (0.135%)

Purpose

Antiseptic

Keep out of reach of children

If swallowed, get medical help or contact a Poison Control Center (1-800-222-1222) right away.

Uses

To decrease bacteria on the skin when soap and water are not available. Recommended for repeated use.

Warnings

For external use only

When using this product avoid contact with eyes. In case of contact with eyes, flush thoroughly with water.

Stop use and ask a doctor if skin irritation or redness develops and lasts.

Keep out of reach of children. If swallowed get medical help or contact a poison control center immediately.

Directions

Spray adequate amount to desired area (clothing or body) at a distance of 6 inches for best result. Avoid spraying onto dark colored clothing.

Inactive Ingredients

Quercus acutissima Sap, Water (Aqua), 1,2-Hexanediol, Propylene Glycol, PEG-60 Hydrogenated Castor Oil, Triethanolamine, Citric Acid, Fragrance (Parfum).